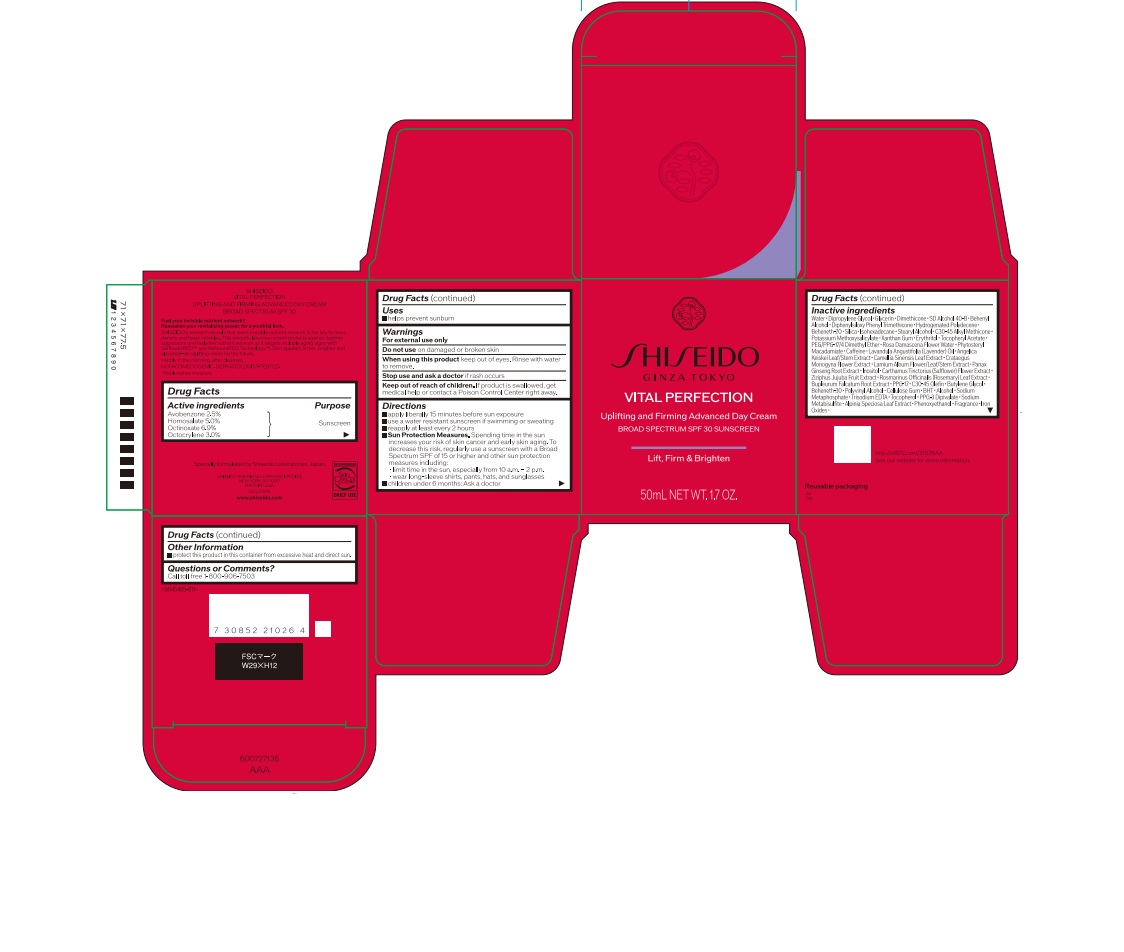 DRUG LABEL: VITAL PERFECTION UPLIFTING AND FIRMING ADVANCED DAY
NDC: 58411-950 | Form: CREAM
Manufacturer: Shiseido Americas Corporation
Category: otc | Type: HUMAN OTC DRUG LABEL
Date: 20260223

ACTIVE INGREDIENTS: AVOBENZONE 1.28 g/50 mL; HOMOSALATE 2.56 g/50 mL; OCTINOXATE 3.53 g/50 mL; OCTOCRYLENE 1.54 g/50 mL
INACTIVE INGREDIENTS: WATER

VITAL PERFECTION UPLIFTING AND FIRMING ADVANCED DAY

Drug Facts

Active Ingredients | Purpose
Avobenzone 2.5% | Sunscreen
Homosalate 5.0% | Sunscreen
Octinoxate 6.9% | Sunscreen
Octocrylene 3.0% | Sunscreen

Uses

- Helps prevent sunburn

Warnings

For external use only

Do not use on damage or broken skin

When using this product keep out of eyes. Rinse with water to remove.

Stop use and ask a doctor if rash occurs

Keep out of reach of children. If product is swallowed, get medical help or contact a Poison Control Center right away.

Directions

- apply liberally 15 minutes before sun exposure
- use a water resistant sunscreen if swimming or sweating
- reapply at least every 2 hours
- Sun Protection Measures. Spending time in the sun increases your risk of skin cancerr and early skin aging. To decrease this rick, regularly use a sunscreen with a Broad Spectru, SPF of 15 or higher and other sun protection measures including:

• limit time in the sun, especially from 10 a.m. - 2 p.m.

• wear long-sleeve shirts, pants, hats, and sunglasses

- Children under 6 months: Ask a doctor

INACTIVE INGREDIENT

Water･Dipropylene Glycol･Glycerin･Dimethicone･SD Alcohol 40-B･Behenyl Alcohol･Diphenylsiloxy Phenyl Trimethicone･Hydrogenated Polydecene･Beheneth-20･Silica･Isohexadecane･Stearyl Alcohol･C30-45 Alkyl Methicone･Potassium Methoxysalicylate･Xanthan Gum･Erythritol･Tocopheryl Acetate･PEG/PPG-17/4 Dimethyl Ether･Rosa Damascena Flower Water･Phytosteryl Macadamiate･Caffeine･Lavandula Angustifolia (Lavender) Oil･Angelica Keiskei Leaf/Stem Extract･Camellia Sinensis Leaf Extract･Crataegus Monogyna Flower Extract･Lamium Album Flower/Leaf/Stem Extract･Panax Ginseng Root Extract･Inositol･Carthamus Tinctorius (Safflower) Flower Extract･Ziziphus Jujuba Fruit Extract･Rosmarinus Officinalis (Rosemary) Leaf Extract･Bupleurum Falcatum Root Extract･PPG-17･C30-45 Olefin･Butylene Glycol･Beheneth-30･Polyvinyl Alcohol･Cellulose Gum･BHT･Alcohol･Sodium Metaphosphate･Trisodium EDTA･Tocopherol･PPG-3 Dipivalate･Sodium Metabisulfite･Alpinia Speciosa Leaf Extract･Phenoxyethanol･Fragrance･Iron Oxides･

Other information

- protect this product in this container from excessibe heat and direct sunlight

Questions or Comments?

Call toll free 1-800-906-7503

PRINCIPAL DISPLAY PANEL - 50 mL Jar Carton

SHISEIDO

Ginza Tokyo

Vital Perfection

Uplifting and Firming Advanced Day Cream

Broad Spectrum SPF 30 Sunscreen

Lift, Firm & Brighten

50mL NET WT. 1.7 OZ.